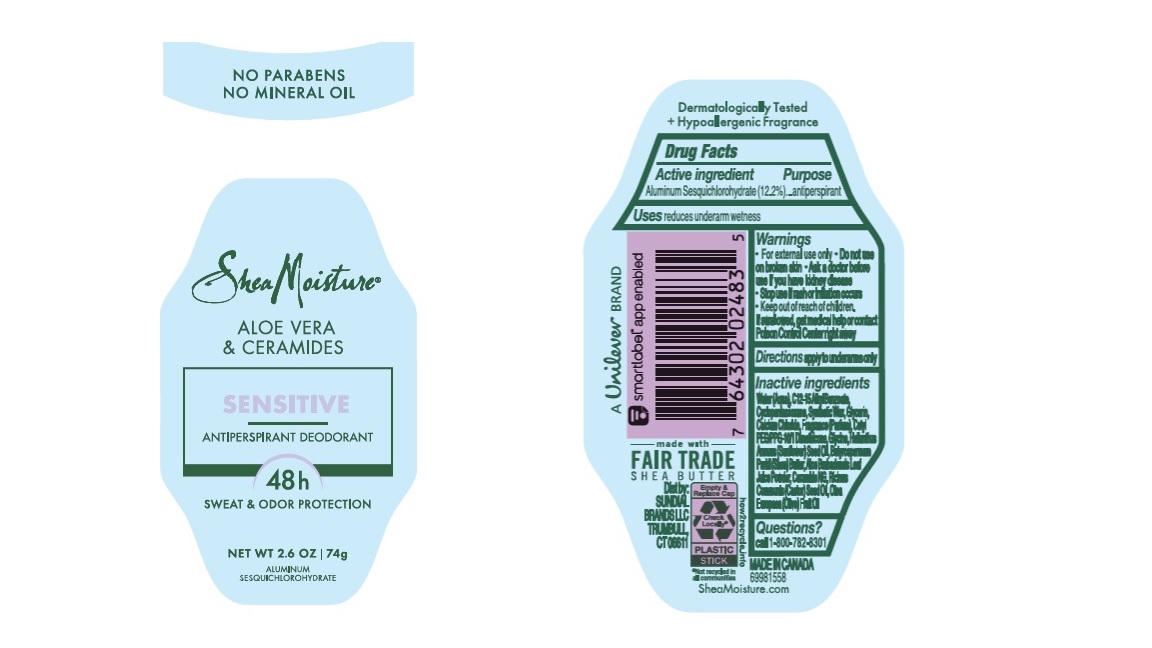 DRUG LABEL: Dove
NDC: 64942-2150 | Form: STICK
Manufacturer: Conopco Inc. d/b/a/ Unilever
Category: otc | Type: HUMAN OTC DRUG LABEL
Date: 20241024

ACTIVE INGREDIENTS: ALUMINUM SESQUICHLOROHYDRATE 12.2 g/100 g
INACTIVE INGREDIENTS: GLYCERIN; CETYL PEG/PPG-10/1 DIMETHICONE (HLB 4); GLYCINE; SHEA BUTTER; CERAMIDE NG; CASTOR OIL; OLIVE OIL; ALKYL (C12-15) BENZOATE; ALOE VERA LEAF; SUNFLOWER OIL; CYCLOMETHICONE 5; CALCIUM CHLORIDE; WATER; SYNTHETIC WAX (1200 MW)

Shea Moisture Aloe Vera & Ceramide Sensitive 48h Antiperspirant Deodorant

Drug Facts

Active ingredient

Aluminum Sesquichlorohydrate (12.2)

Purpose

antiperspirant

Uses

reduces underarm wetness

Warnings

• For external use only.
• Do not use on broken skin .
• Ask a doctor before use if you have kidney disease.
• Stop use if rash or irritation occurs.

• Keep out of reach of children.

If swallowed, get medical help or contact a Poison Control Center right away.

Directions

apply to underarms only

Inactive ingredients

Water (Aqua), C12-15 Alkyl Benzoate, Cyclopentasiloxane, Synthetic Wax, Glycerin, Calcium Chloride, Fragrance (Parfum), Cetyl PEG/PPG-10/1 Dimethicone, Glycine, Helianthus Annuus (Sunflower) Seed Oil, Butyrospermum Parkii (Shea) Butter, Aloe Barbadensis Leaf Juice Powder, Ceramide NG, Ricinus Communis (Castor) Seed Oil, Olea Europaea (Olive) Fruit Oil

Questions?

Call 1-800-761-3683